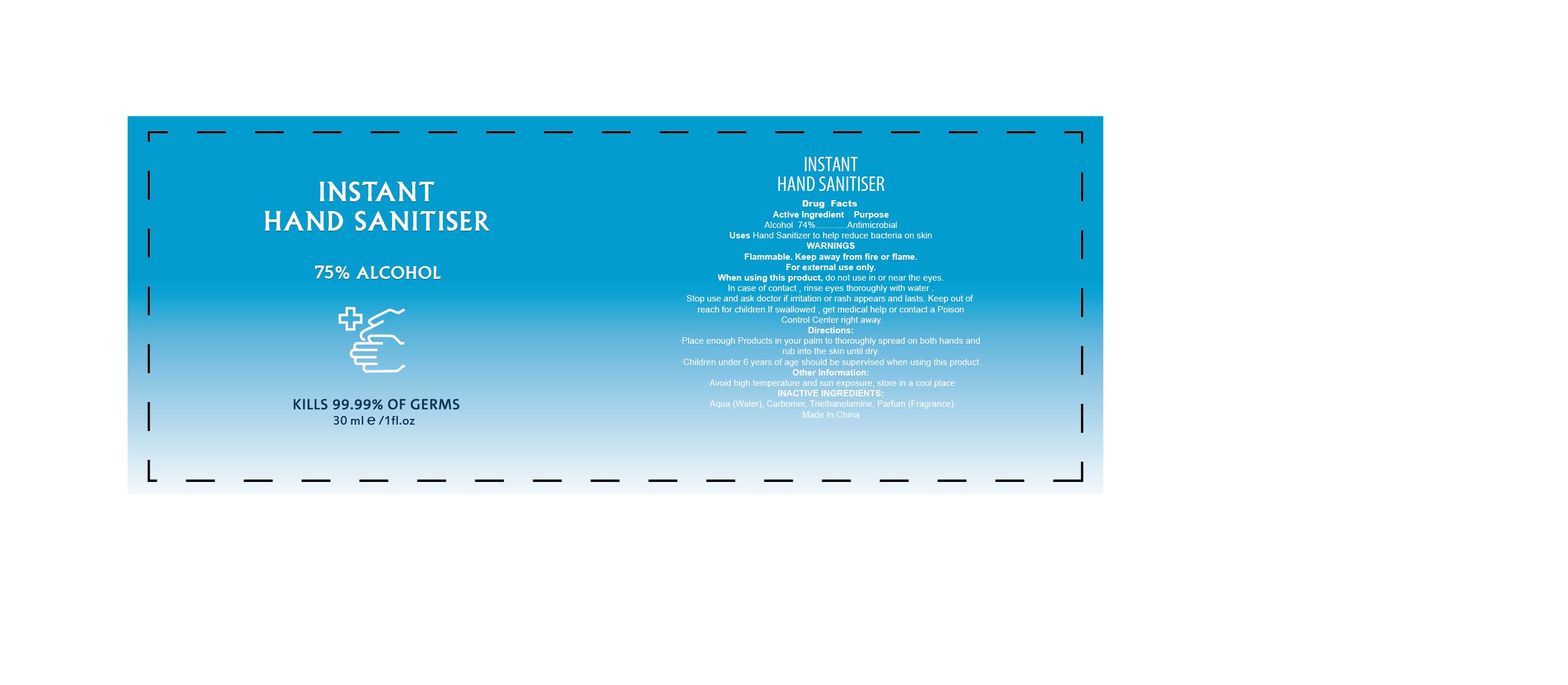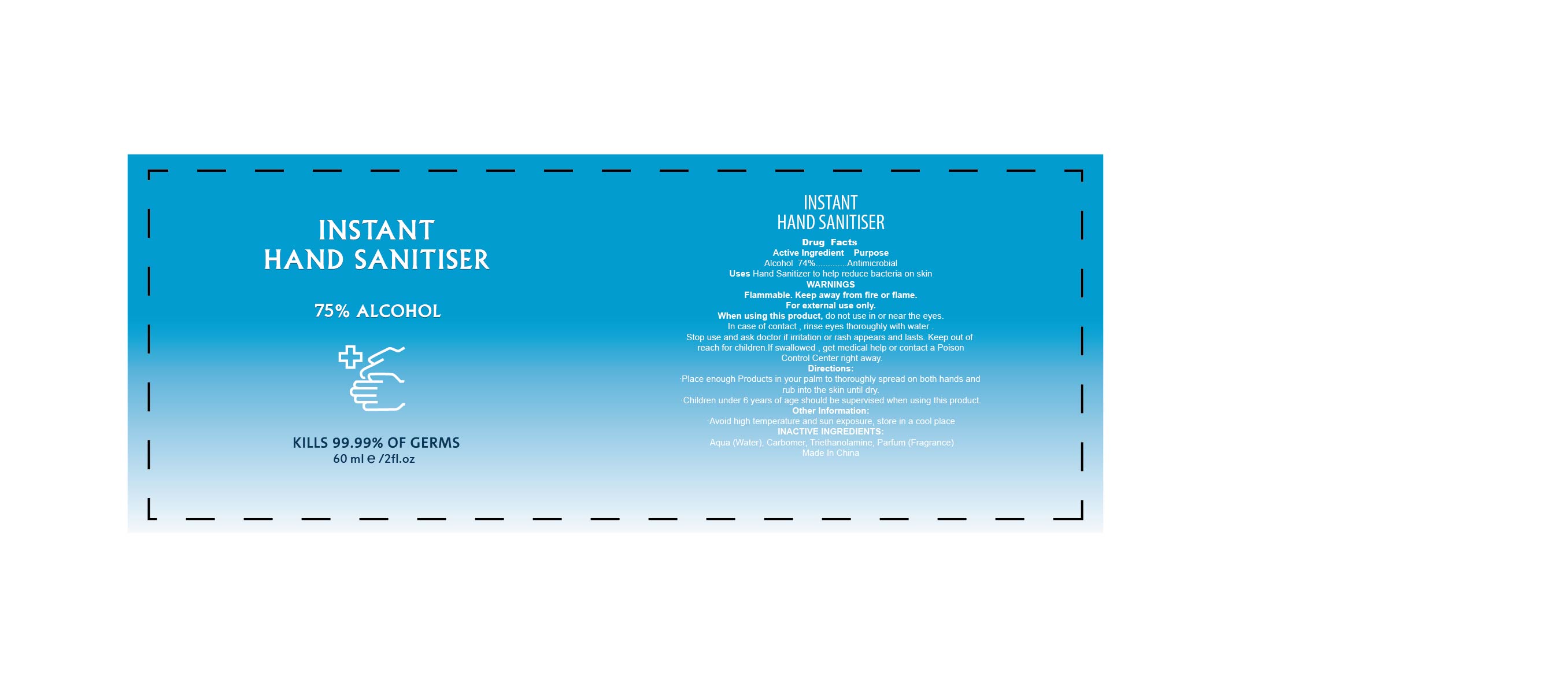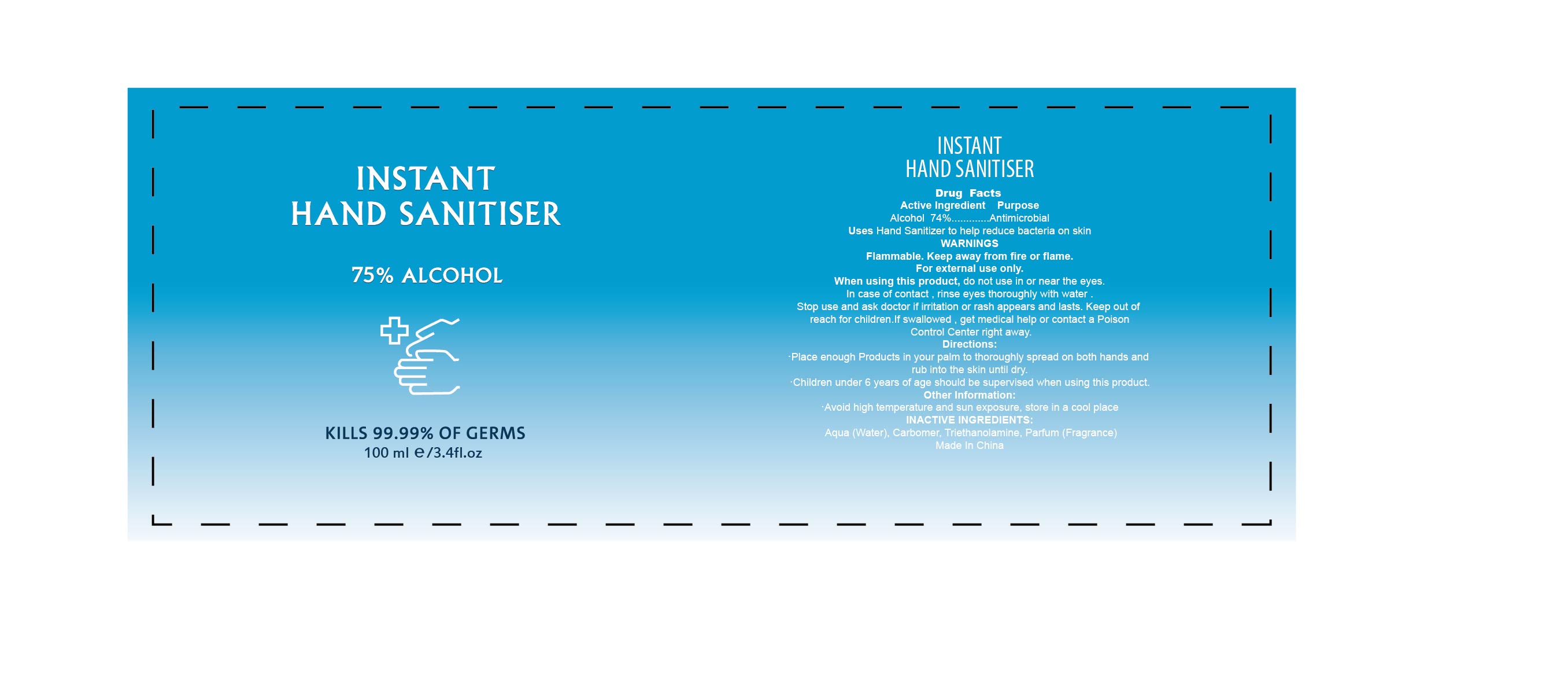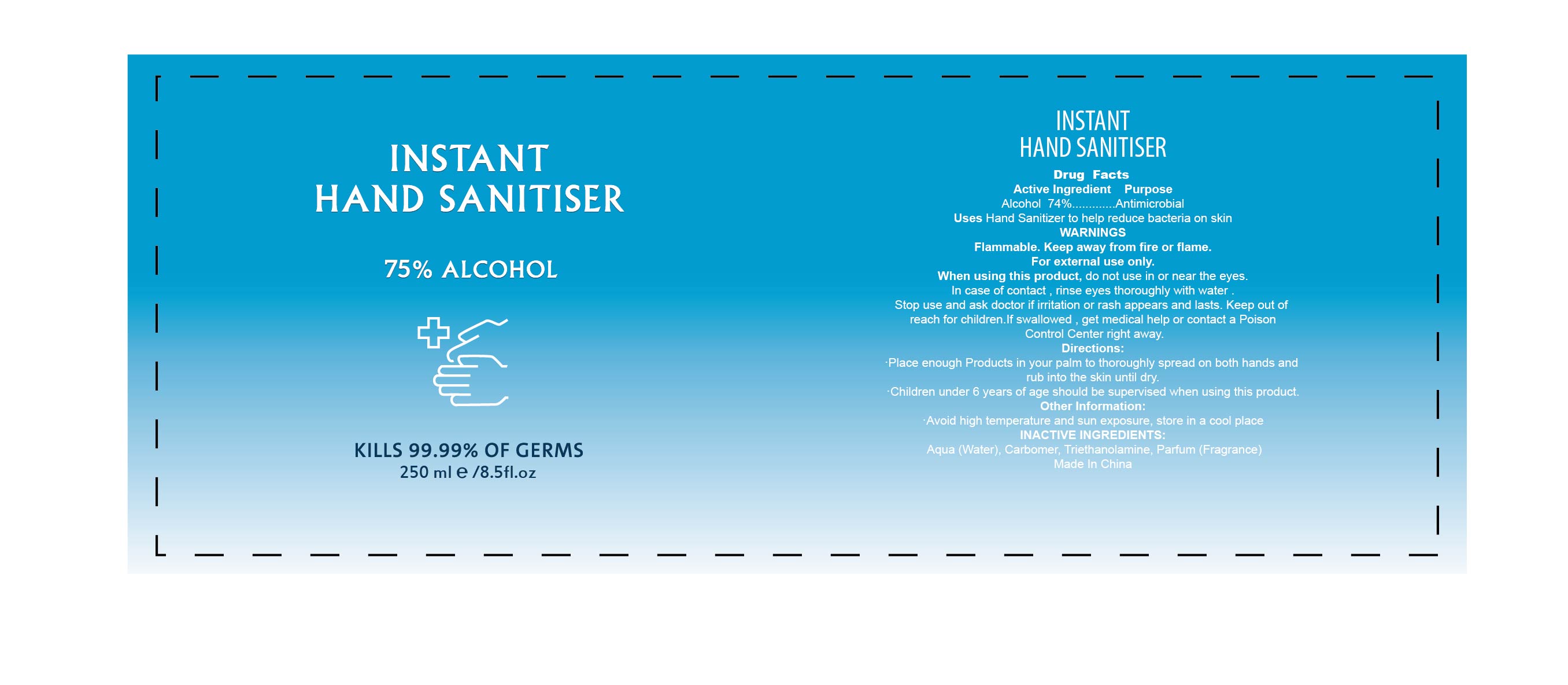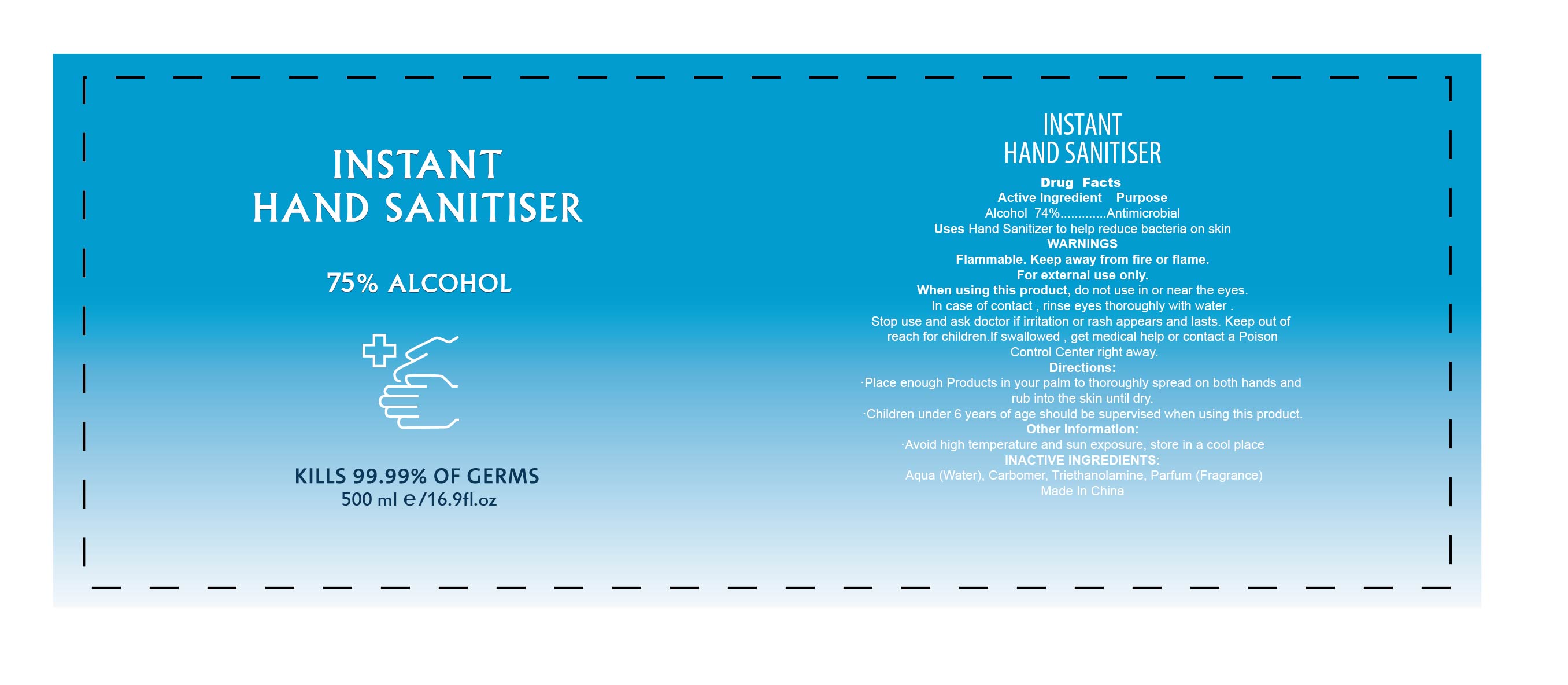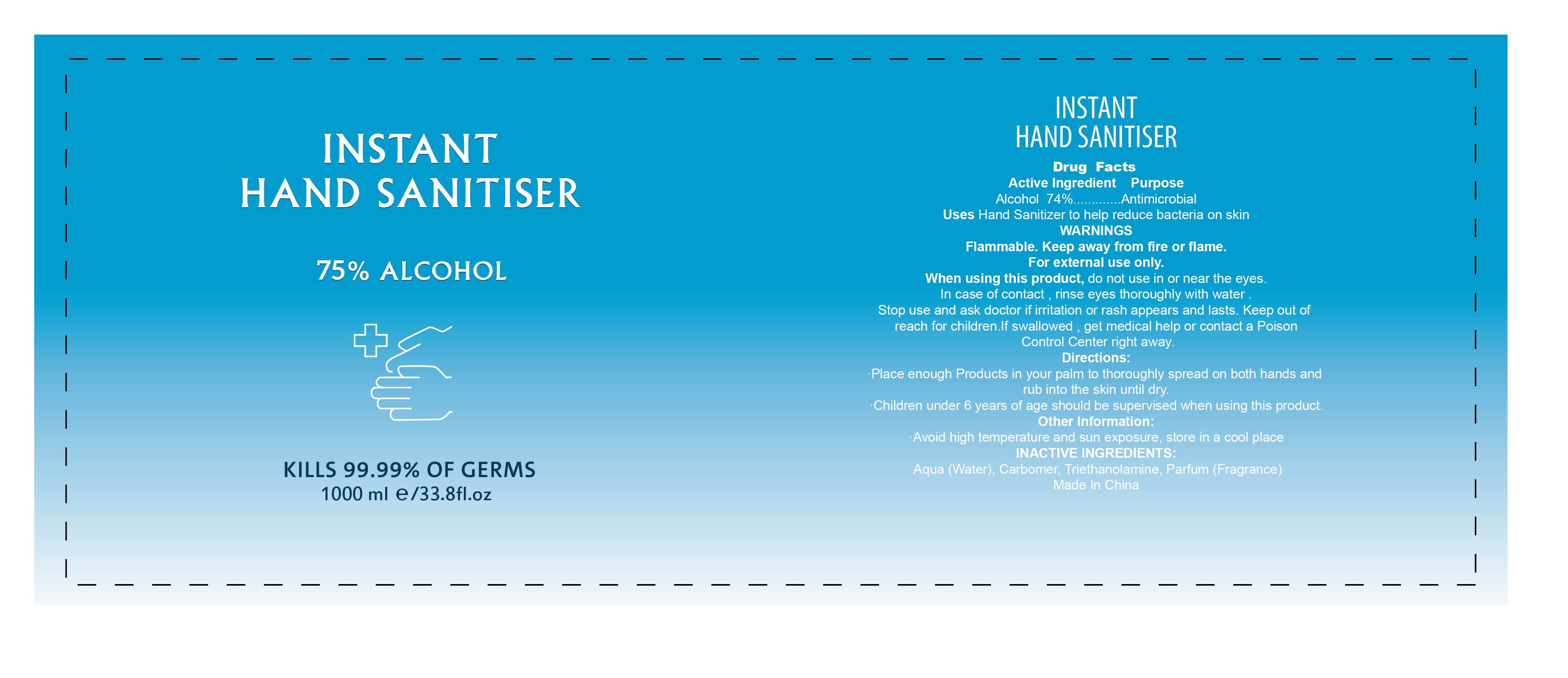 DRUG LABEL: INSTANT HAND SANITISER
NDC: 74440-001 | Form: GEL
Manufacturer: Jiangxi Iris Chemical Co.,ltd
Category: otc | Type: HUMAN OTC DRUG LABEL
Date: 20200413

ACTIVE INGREDIENTS: ALCOHOL 74 mL/100 mL
INACTIVE INGREDIENTS: TROLAMINE; FRAGRANCE LAVENDER & CHIA F-153480; WATER; CARBOMER HOMOPOLYMER, UNSPECIFIED TYPE

INSTANT HAND SANITISER

Active Ingredient

Alcohol 74%

Purpose

Antimicrobial

Uses

Hand Sanitizer to help reduce bacteria on skin.

WARNINGS

Flammable. Keep away from fire or flame.For external use only.

When using this product

do not use in or near the eyes.In case of contact,rinse eyes thoroughly with water.Stop use and ask doctor if irritation or rash appears and lasts.Keep out of reach for children. if swallowed,get medical help or contact a Poison Control Center right away.

Directions

Place enough Products in your palm to thoroughly spread on both hands and rub into the skin until dry.

Children under 6 years of age should be supervised when using this product.

Other information

Avoid high temperature and sun exposure ,store in a cool place.

INACTIVE INGREDIENTS

Aqua(Water),Carbomer,Triethanolamine,Parfum(Fragrance)